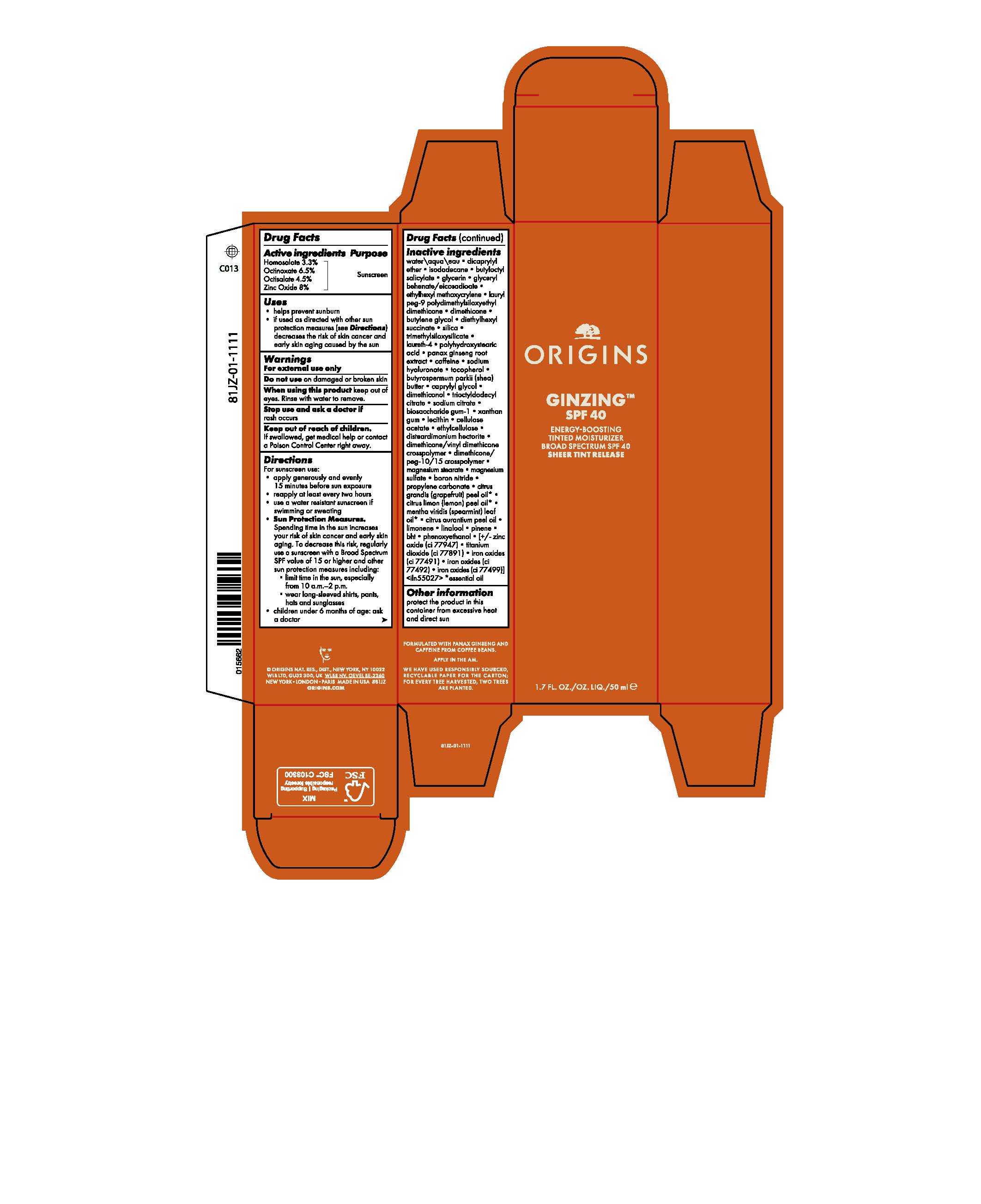 DRUG LABEL: GINZING SPF 40 ENERGY-BOOSTING TINTED MOISTURIZER BROAD SPECTRUM SPF 40 SHEER TINT RELEASE
NDC: 59427-119 | Form: LIQUID
Manufacturer: ORIGINS NATURAL RESOURCES INC.
Category: otc | Type: HUMAN OTC DRUG LABEL
Date: 20260112

ACTIVE INGREDIENTS: OCTINOXATE 65 mg/1 mL; HOMOSALATE 33 mg/1 mL; OCTISALATE 45 mg/1 mL; ZINC OXIDE 80 mg/1 mL
INACTIVE INGREDIENTS: POLYHYDROXYSTEARIC ACID (2300 MW); XANTHAN GUM; MAGNESIUM STEARATE; SODIUM HYALURONATE; SODIUM CITRATE; DIMETHICONE/VINYL DIMETHICONE CROSSPOLYMER (HARD PARTICLE); BORON NITRIDE; PROPYLENE CARBONATE; CELLULOSE ACETATE; LIMONENE, (+)-; DIMETHICONE/PEG-10/15 CROSSPOLYMER; CITRUS GRANDIS (GRAPEFRUIT) PEEL OIL; MENTHA VIRIDIS (SPEARMINT) LEAF OIL; CI 77891; BIOSACCHARIDE GUM-1; PHENOXYETHANOL; CI 77491; CI 77492; CI 77499; DIMETHICONE; WATER; BUTYLOCTYL SALICYLATE; ETHYLCELLULOSE; MAGNESIUM SULFATE; LINALOOL; LAURYL PEG-9 POLYDIMETHYLSILOXYETHYL DIMETHICONE; GLYCERIN; DICAPRYLYL ETHER; ISODODECANE; GLYCERYL BEHENATE/EICOSADIOATE; ETHYLHEXYL METHOXYCRYLENE; BUTYLENE GLYCOL; PANAX GINSENG ROOT; SOYBEAN LECITHIN; CITRUS LIMON (LEMON) PEEL OIL; CITRUS AURANTIUM AMARA (BITTER ORANGE) PEEL OIL; LAURETH-4; CAPRYLYL GLYCOL; DISTEARDIMONIUM HECTORITE; BUTYROSPERMUM PARKII (SHEA) BUTTER; TRIOCTYLDODECYL CITRATE; DIETHYLHEXYL SUCCINATE; SILICA; TRIMETHYLSILOXYSILICATE (M/Q 0.6-0.8); TOCOPHEROL; DIMETHICONOL (2000 CST); BHT; CAFFEINE; PINENE

GINZING SPF 40 ENERGY-BOOSTING TINTED MOISTURIZER BROAD SPECTRUM SPF 40 SHEER TINT RELEASE

Active ingredients

HOMOSALATE 9.00%
OCTINOXATE 6.50%
OCTISALATE 4.50%
ZINC OXIDE 8.00%

Purpose

Sunscreen

Uses

- helps prevent sunburn
- if used as directed with other sun protection measures (see Diredions) decreases the risk of skin cancer and early skin aging caused by the sun

Warnings

For external use only

Do not use

on damaged or broken skin

When using this product

keep out of eyes. Rinse with water to remove

Stop use and ask a doctor if

rash occurs

Keep out of reach of children

If swallowed, get medical help or contact a Poison Control Center right away

Directions

For sunscreen use:
• apply generously and evenly
15 minutes before sun exposure

- reapply at least every two hours

use a water resistant sunscreen if
swimming or sweating

- Sun Protection Measures.

Spending time in the sun increases
your risk of skin cancer and early skin
aging. To decrease this risk, regularly
use a sunscreen with a Brood Spectrum
SPF value of 15 or higher ond other
sun protection meosures including:
• limit time in the sun, especially
from 10 o.m.-2 p.m.
• wear long-sleeved shirts, pants,
hots and sunglasses

- children under 6 months of age: ask

a doctor

Inactive ingredients

water\aqua\eau • dicoprylyl ether • isododecane • butyloctyl solicylate • glycerin • glyceryl behenate/ eicosodioate •
ethylhexyl methoxycrylene • lauryl peg-9 polydimethylsiloxyethyl dimethicone • dimethicone • butylene glycol • diethylhexyl
succinate • silica • trimethylsiloxysilicote • laureth-4 • polyhydroxysteoric acid • panax ginseng root extract • caffeine • sodium
hyoluronote • tocopherol • butyrospermum parkii (shea) butter • coprylyl glycol • dimethiconol • trioctyldodecyl citrate • sodium citrate • biosocchoride gum-1 • xanthan gum • lecithin • cellulose acetate • ethylcellulose • disteordimonium hectorite • dimethicone/vinyl dimethicone crosspolymer • dimethicone/peg-10/15 crosspolymer • magnesium steorote • magnesium sulfate • boron nitride •
propylene carbonate • citrus grandis (grapefruit) peel oil* • citrus limon (lemon) peel oil* • mentho viridis (spearmint) leaf
oil* • citrus ourantium peel oil • limonene • linolool • pinene • bht • phenoxyethanol • [+/-zinc oxide (ci 77947) • titanium
dioxide (ci 77891) • iron oxides (ci 77491) • iron oxides (ci 77492) • iron oxides (ci 77499)]
<iln55027> * essential oil

Other information

protect the product in this container from excessive heat and direct sun

PACKAGE LABEL

ORIGINS

GINZING

SPF 40

ENERGY-BOOSTING

TINTED MOISTURIZER

BROAD SPECTRUM SPF 40

SHEER TINT RELEASE

1.7 FL. OZ./OZ/ LIQ./50 ml e